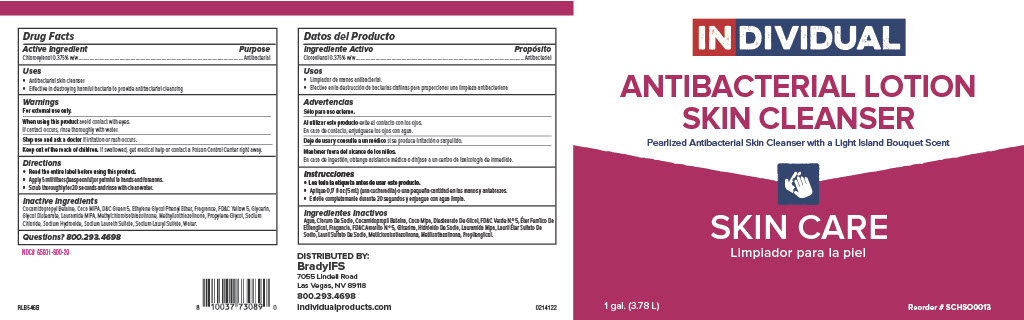 DRUG LABEL: Individual AntibacterialLotion Skin Cleanser
NDC: 79258-141 | Form: SOAP
Manufacturer: Brady Industries Inc.
Category: otc | Type: HUMAN OTC DRUG LABEL
Date: 20220302

ACTIVE INGREDIENTS: CHLOROXYLENOL 3.75 mg/1 mL
INACTIVE INGREDIENTS: LAURIC ISOPROPANOLAMIDE; PROPYLENE GLYCOL; ETHYL ACETOACETATE; DIMETHYL BENZYL CARBINYL ACETATE; GLYCOL DISTEARATE; BENZYL BENZOATE; MAGNESIUM NITRATE; COCAMIDOPROPYL BETAINE; D&C GREEN NO. 5; CHLOROACETIC ACID; LINALOOL, (+/-)-; ETHYL METHYLPHENYLGLYCIDATE; SODIUM CARBONATE; METHYLISOTHIAZOLINONE; SODIUM LAURYL SULFATE; FD&C YELLOW NO. 5; WATER; SODIUM FERROCYANIDE; DIOXANE; ETHYL BUTYRATE; COCO DIETHANOLAMIDE; METHYLCHLOROISOTHIAZOLINONE; IONONE; ETHYLENE OXIDE; TRIBASIC CALCIUM PHOSPHATE; CALCIUM SILICATE; METHYL ALCOHOL; PHENOXYETHANOL; GLYCERIN; LAURIC DIETHANOLAMIDE; SODIUM HYDROXIDE; .GAMMA.-DECALACTONE; METHYL ANTHRANILATE; SODIUM ALUMINIUM SILICATE; MYRCENE

Individual Antibacterial Lotion Skin Cleanser

Active ingredient

Chloroxylenol 0.375% w/w

Uses

Antibacterial skin cleanser

Effective in destroying harful bacteria to prevent antibacterial cleansing

Warnings

For external use only.

When using this product avoid contact with eyes. If contact occurs, rinse thoroughly with water.

Stop use and ask a doctor if irritation or rash occurs.

Keep out of the reach of children. If swallowed, get medical help or contact a Poison Control Center right away.

Directions

Read entire label before using this product.

Apply 5 milliliters (teaspoonful) or palmful to hands and forearms.

Scrub thoroughly for 20 seconds and rinse with clean water.

Inactive Ingredients

Cocamidopropyl Betaine, Coco MIPA, D&C Green 5, Ethylene Glycol Phenyl Ether, Fragrance, FD&C Yellow 5, Glycerin, Glycol Distearate, Lauramide MIPA, Methylchloroisothiazolinone, Methylisothiazolinone, Propylene Glycol, Sodium Chloride, Sodium Hydroxide, Sodium Laureth Sulfate, Sodium Lauryl Sulfate, Water.

Purpose

Antibacterial

Keep out of reach of children

Keep out of the reach of children